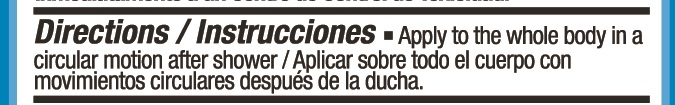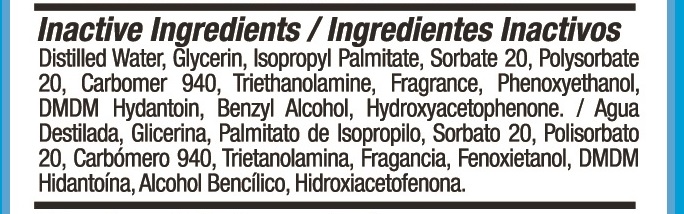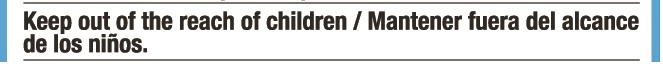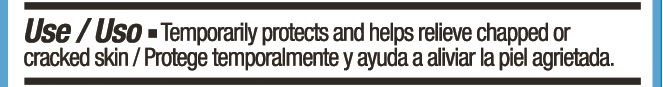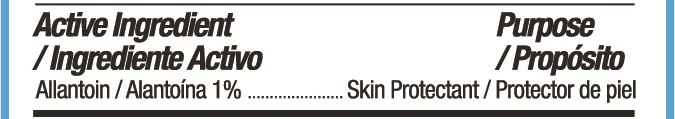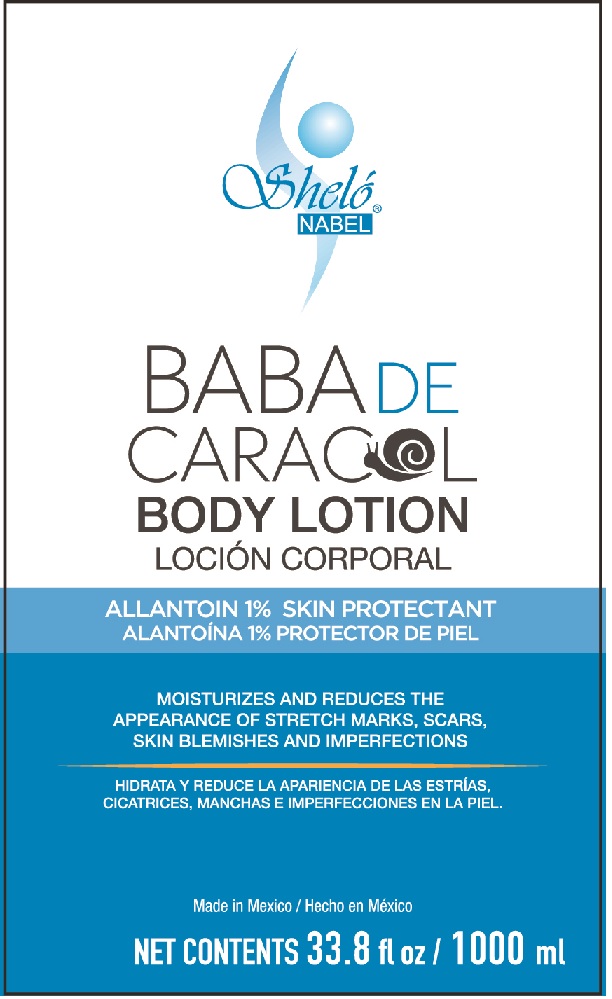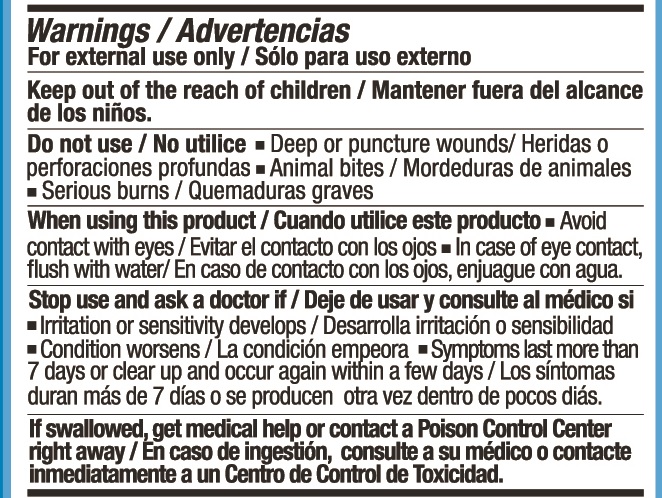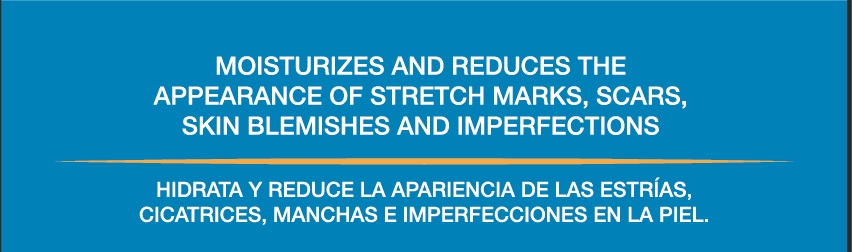 DRUG LABEL: Shelo NABEL Baba de Caracol Locion Corporal
NDC: 71424-1156 | Form: CREAM
Manufacturer: Corporativo Serysi S de R L de C V
Category: otc | Type: HUMAN OTC DRUG LABEL
Date: 20191015

ACTIVE INGREDIENTS: ALLANTOIN 10 mg/1 g
INACTIVE INGREDIENTS: GLYCERIN

Sheló NABEL Baba de Caracol Loción Corporal